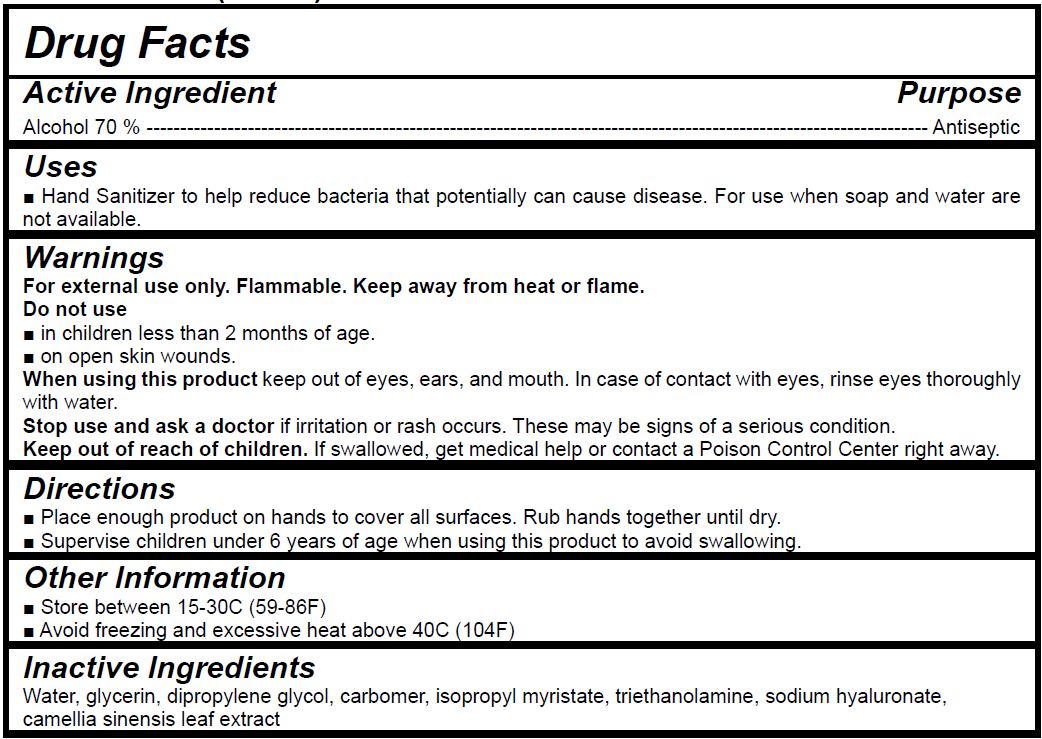 DRUG LABEL: Purus hand sanitizer gel
NDC: 77504-0002 | Form: GEL
Manufacturer: The fab Korea Co., Ltd.
Category: otc | Type: HUMAN OTC DRUG LABEL
Date: 20200603

ACTIVE INGREDIENTS: ALCOHOL 1085 mL/1550 mL
INACTIVE INGREDIENTS: WATER; GLYCERIN; DIPROPYLENE GLYCOL; CARBOMER HOMOPOLYMER, UNSPECIFIED TYPE; ISOPROPYL MYRISTATE; TROLAMINE; HYALURONATE SODIUM; GREEN TEA LEAF

The fab Korea Co., Ltd. - Purus hand sanitizer gel 1550ml

ACTIVE INGREDIENT

Alcohol

INACTIVE INGREDIENT

water, glycerin, dipropylene glycol, carbomer, isopropyl myristate, triethanolamine, sodium hyaluronate, camellia sinensis leaf extract

PURPOSE

Hand sanitizer to help reduce bacteria that potentially can cause disease. For use when soap and water are not available.

keep out of reach of the children

INDICATIONS AND USAGE

Place enough product on hands to cover all surfaces. Rub hands together until dry.

Supervise children under 6 years of age when using this product to avoid swallowing.

WARNINGS

For external use only. Flammable. Keep away from heat or flame.

Do not use

- in children less than 2 months of age
- on open skin wounds

When using this product keep out of eyes, ears, and mouth. In case of contact with eyes, rinse thoroughly with water.

Stop use and ask a doctor if irritation or rash occurs. These may be signs of a serious condition.

Keep out of reach of children. If swallowed, get medical help or contact a Poison Control Center right away.

DOSAGE AND ADMINISTRATION

for external use only